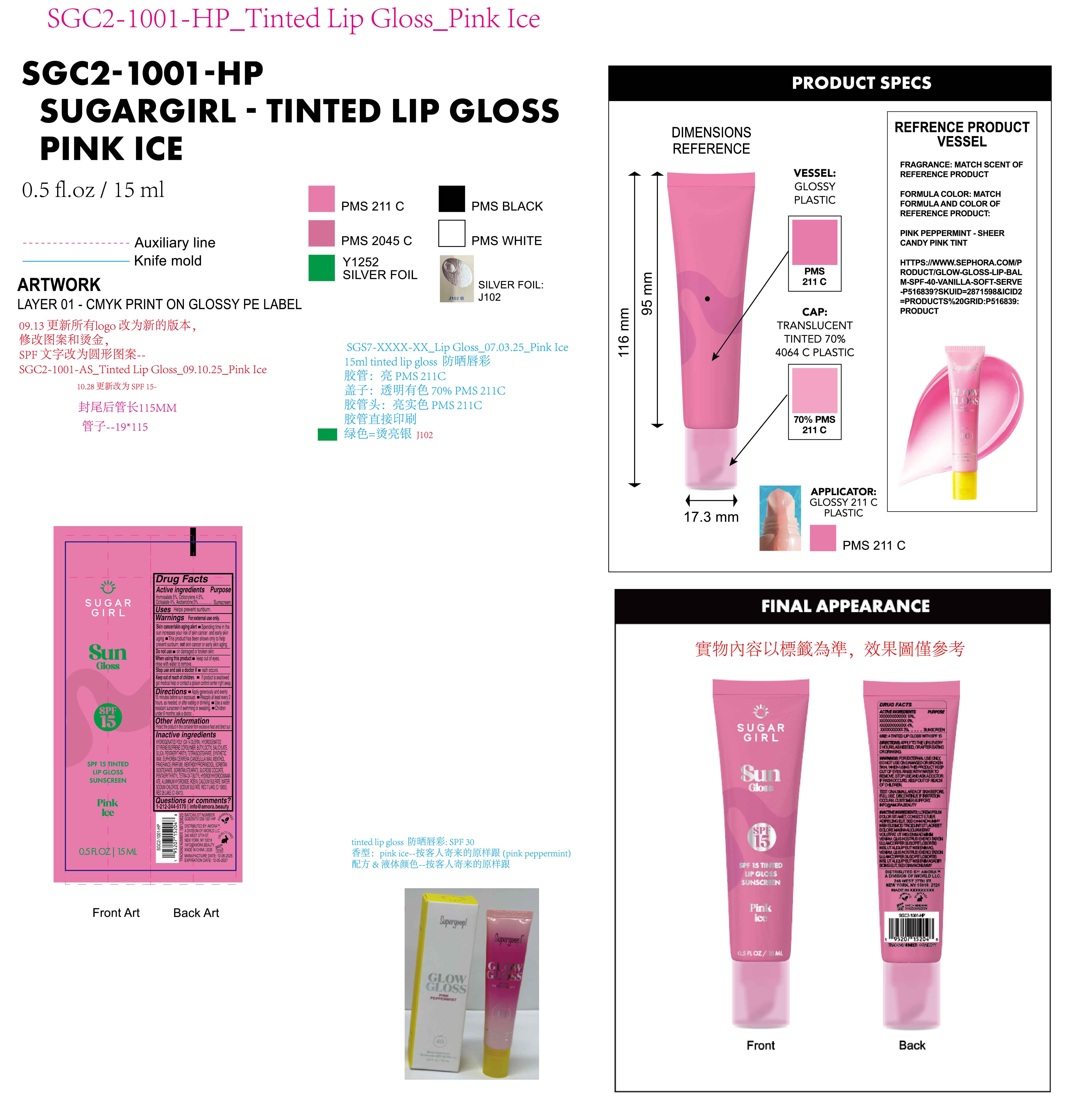 DRUG LABEL: Sugargirl sun gloss SPF15 tinted lip gloss Sunscreen Pink Ice
NDC: 85161-152 | Form: GEL
Manufacturer: Longway Technology(Guangzhou)Co.,Ltd.
Category: otc | Type: HUMAN OTC DRUG LABEL
Date: 20251204

ACTIVE INGREDIENTS: OCTOCRYLENE 0.045 g/1 mL; AVOBENZONE 0.03 g/1 mL; HOMOSALATE 0.05 g/1 mL; ETHYLHEXYL SALICYLATE 0.04 g/1 mL
INACTIVE INGREDIENTS: CALCIUM SULFATE; SODIUM CHLORIDE; MENTHOXYPROPANEDIOL; SILICA; CI 15850; PENTAERYTHRITYL TETRAISOSTEARATE; SYNTHETIC WAX (540 MW); ALUMINUM HYDROXIDE; ROSIN; PENTAERYTHRITYL TETRA-DI-T-BUTYL HYDROXYHYDROCINNAMATE; SORBITAN STEARATE; STYRENE/ISOPRENE COPOLYMER (28:72; 210000 MW); CI 45410; SUCROSE COCOATE; SODIUM SULFATE; SORBITAN ISOSTEARATE; WATER; MENTHOL; BUTYLOCTYL SALICYLATE; EUPHORBIA CERIFERA (CANDELILLA) WAX; HYDROGENATED POLY(C6-14 OLEFIN; 4 CST); FRAGRANCE 13576

ACTIVE INGREDIENT

Homosalate 5%, Octocrylene 4.5%, Octisalate 5% , Avobenzone 3%

PURPOSE

Sunscreen

QUESTIONS

1-212-244-5170 info@amora.beauty

OTHER SAFETY INFORMATION

Protect the product in this container from excessive heat and direct sun.

INDICATIONS AND USAGE

Helps prevent sunburn.

DOSAGE AND ADMINISTRATION

Apply generously and evenly15 minutes before sun exposure.

Reapply at least every 2hours, as needed. or after eating or drinking.

Use a water resistant sunscreen if swimming or sweating.

Chidren under 6 months. ask a doctor.

Warnings

For external use only.
Skin cancer/skin aging alert.

Spending time in the sun increases your risk of skin cancer and early skin aging.

This product has been shown only to help prevent sunburn, not skin cancer or early skin aging.

Do not use on damaged or broken skin.

When using this product . keep out of eyes. rinse with water to remove.

Stop use and ask a doctor if rash occurs.

Keep out of reach of children. lf product is swallowed get medical help or contact a poison control center right away

Keep out of reach of children.

lf product is swallowed get medical help or contact a poison control center right away

INACTIVE INGREDIENT

HYDROGENATED POLY(C6-14 OLEFIN), HYDROGENATED STYRENE/ISOPRENE COPOLYMER, BUTYLOCTYL SALICYLATE, SILICA,PENTAERYTHRITYL TETRAISOSTEARATE,SYNTHETIC WAX, EUPHORBIA CERIFERA (CANDELILLA) WAX,MENTHOL,FRAGRANCE (PARFUM),MENTHOXYPROPANEDIOL,SORBITAN ISOSTEARATE,SORBITAN STEARATE,SUCROSE COCOATE,PENTAERYTHRITYL TETRA-DI-t-BUTYL HYDROXYHYDROCINNAMATE,ALUMINUM HYDROXIDE,ROSIN,CALCIUM SULFATE,WATER,SODIUM CHLORIDE,SODIUM SULFATE, RED 7 LAKE(C) 15850) , RED 28 LAKE (CI 45410)